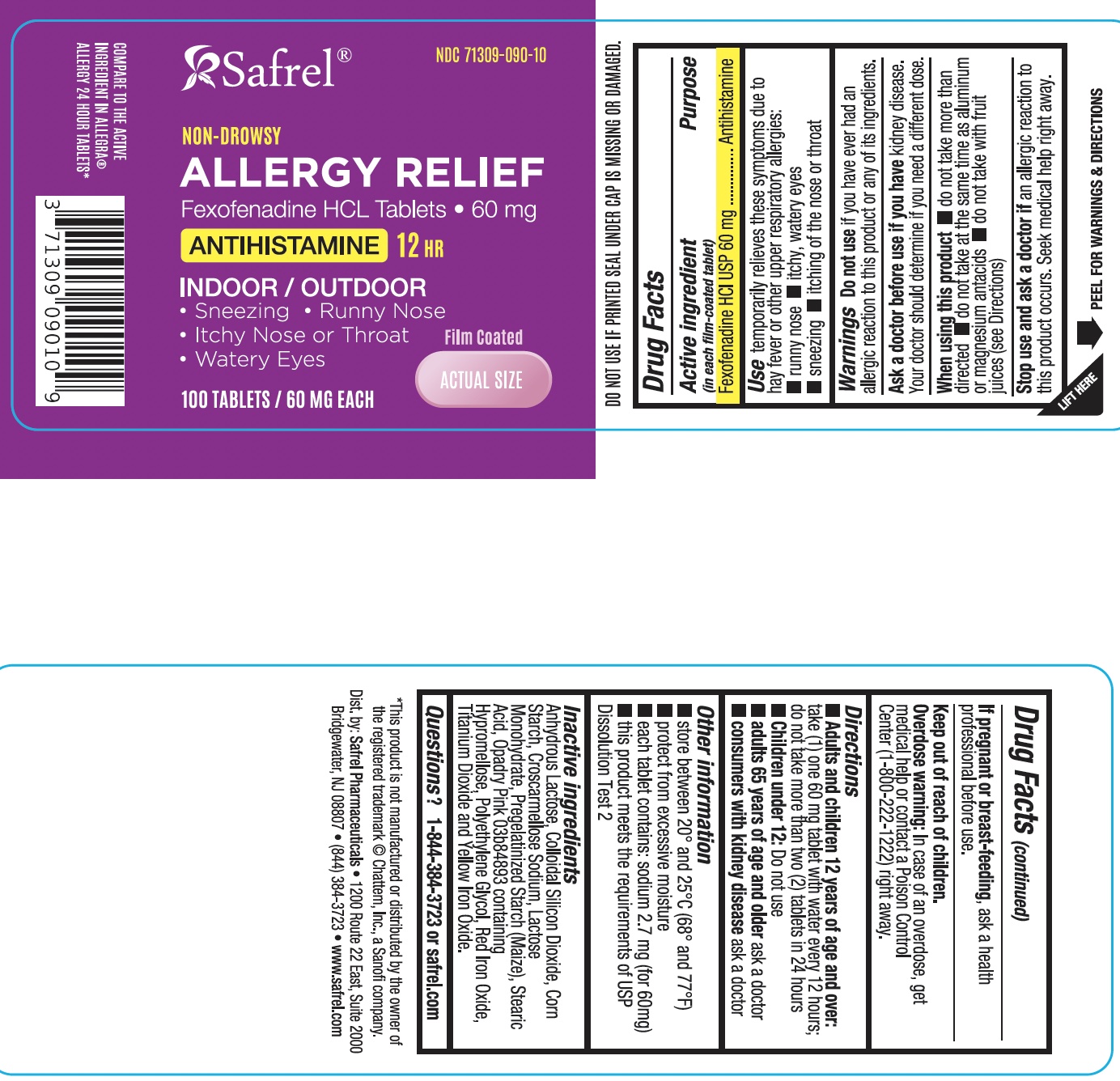 DRUG LABEL: Fexofenadine HCl
NDC: 71309-090 | Form: TABLET, FILM COATED
Manufacturer: Safrel Pharmaceuticals, LLC.
Category: otc | Type: HUMAN OTC DRUG LABEL
Date: 20230731

ACTIVE INGREDIENTS: FEXOFENADINE HYDROCHLORIDE 60 mg/1 1
INACTIVE INGREDIENTS: ANHYDROUS LACTOSE; SILICON DIOXIDE; STARCH, CORN; CROSCARMELLOSE SODIUM; LACTOSE MONOHYDRATE; STEARIC ACID; HYPROMELLOSE, UNSPECIFIED; POLYETHYLENE GLYCOL, UNSPECIFIED; FERRIC OXIDE RED; TITANIUM DIOXIDE; FERRIC OXIDE YELLOW

FEXOFENADINE HYDROCHLORIDE TABLETS USP, 60mg and 180 mg
Allergy

ALLERGY Active ingredient (in each film-coated tablet)

Fexofenadine HCl USP, 60mg

Purpose

Antihistamine

Uses

temporarily relieves these symptoms due to hay fever or other upper respiratory allergies:

- runny nose
- itchy, watery eyes
- sneezing
- itching of the nose or throat

Warnings

Do not use

if you have ever had an allergic reaction to this product or any of its ingredients.

Ask a doctor before use if you have

kidney disease. Your doctor should determine if you need a different dose.

When using this product

- do not take more than directed
- do not take at the same time as aluminum or magnesium antacids
- do not take with fruit juices (see Directions)

Stop use and ask a doctor if

an allergic reaction to this product occurs. Seek medical help right away.

If pregnant or breast-feeding,

ask a health professional before use.

Keep out of reach of children.

In case of overdose, get medical help or contact a Poison Control Center right away (1800-222-1222).

Directions

FOR 60mg

adults and children 12 years of age and over

take two 60mg tablets with water evrery 12 hours; do not take more than 2 tablets in 24 hours

children under 12 years of age

do not use

adults 65 years of age and older

ask a doctor

consumers with kidney disease

ask a doctor

Other information

- safety sealed: do not use if carton is opened or if printed foil inner seal on bottle is torn or missing
- store between 20° and 25°C (68° and 77°F)
- protect from excessive moisture

Inactive ingredients

anhydrous lactose, colloidal silicon dioxide, corn starch, croscarmellose sodium, lactose monohydrate, pregelatinized starch (maize), stearic acid, opadry pink 03B84893 containing hypromellose, polyethylene glycol, red iron oxide, titanium dioxide and yellow iron oxide.

Questions or comments?

Call 1-844-384-3723

Distributed by:
Safrel Pharmaceuticals, LLC

Bridgewater, NJ 08807

www.safrel.com